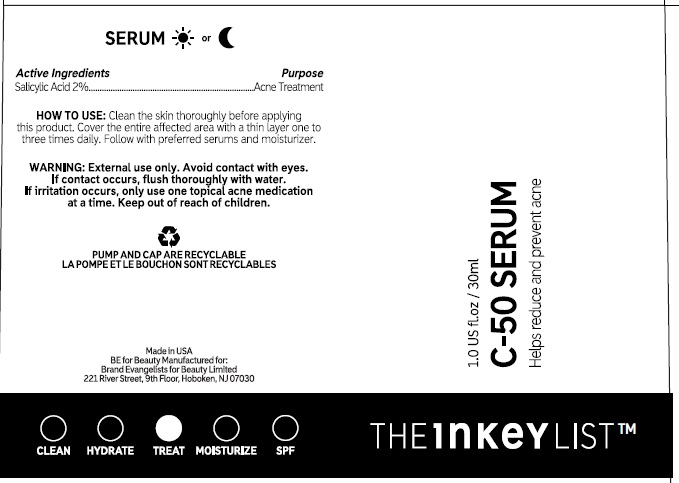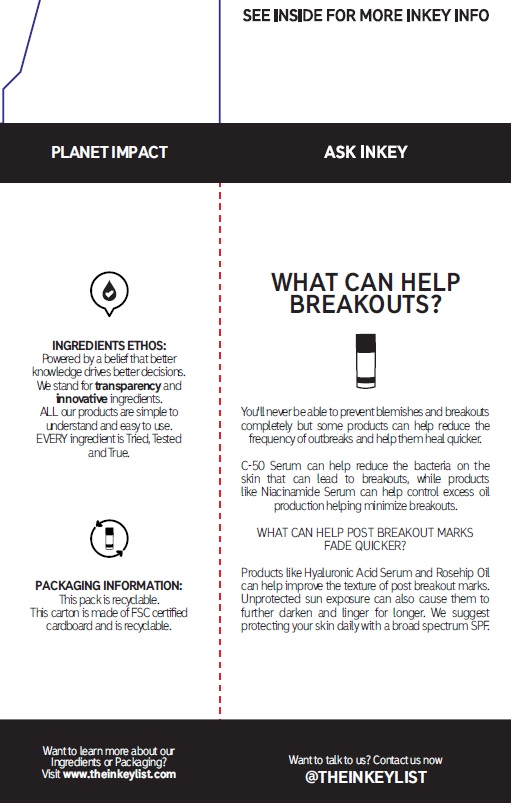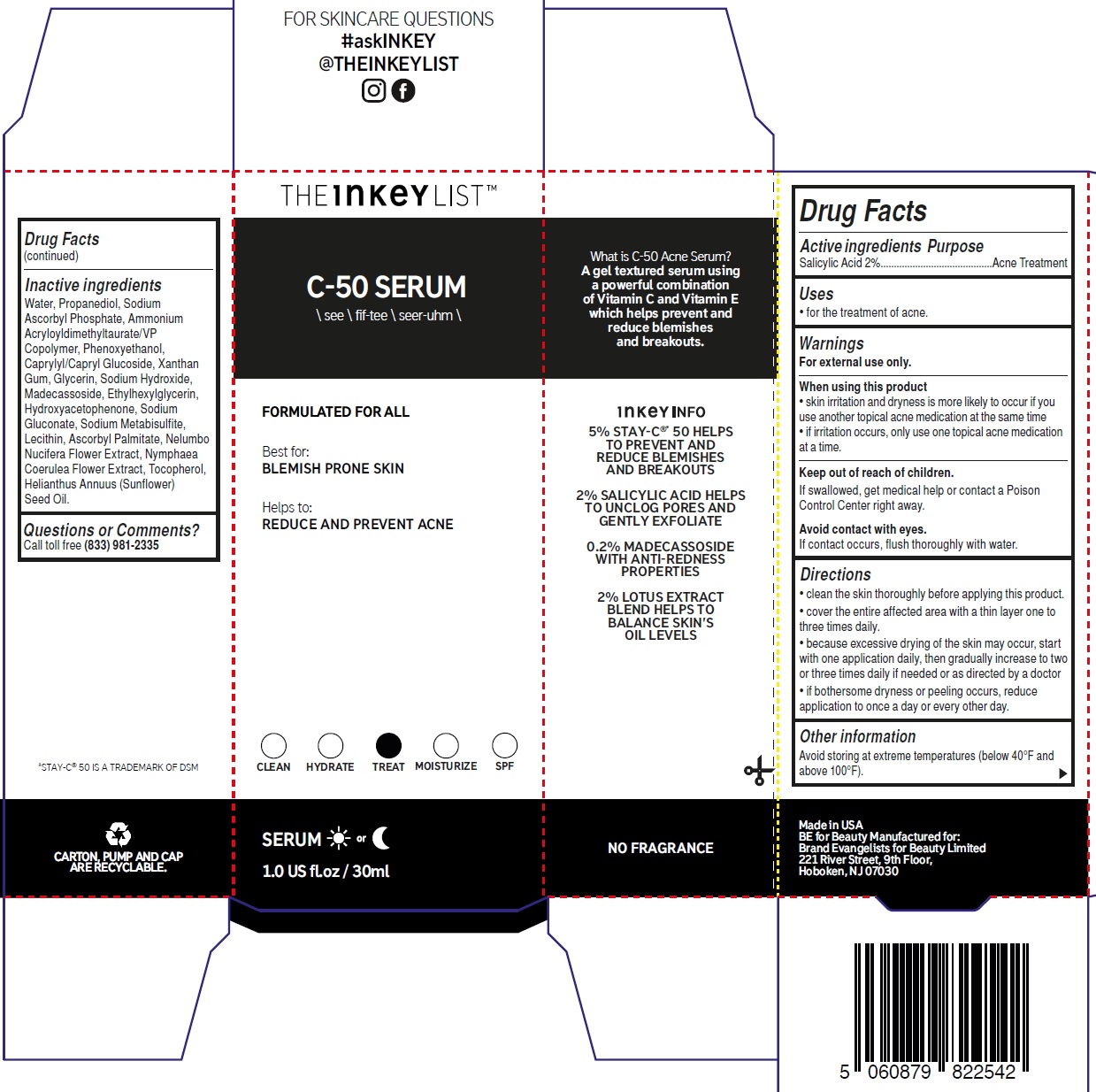 DRUG LABEL: The INKEY List C 50 Serum
NDC: 81136-020 | Form: GEL
Manufacturer: Brand Evangelists for Beauty Ltd
Category: otc | Type: HUMAN OTC DRUG LABEL
Date: 20240226

ACTIVE INGREDIENTS: SALICYLIC ACID 20 mg/1 mL
INACTIVE INGREDIENTS: LECITHIN, SOYBEAN; WATER; PROPANEDIOL; SODIUM ASCORBYL PHOSPHATE; AMMONIUM ACRYLOYLDIMETHYLTAURATE/VP COPOLYMER; PHENOXYETHANOL; CAPRYLYL/CAPRYL OLIGOGLUCOSIDE; XANTHAN GUM; GLYCERIN; SODIUM HYDROXIDE; MADECASSOSIDE; ETHYLHEXYLGLYCERIN; HYDROXYACETOPHENONE; SODIUM GLUCONATE; SODIUM METABISULFITE; ASCORBYL PALMITATE; NELUMBO NUCIFERA FLOWER; NYMPHAEA CAERULEA FLOWER; TOCOPHEROL; SUNFLOWER OIL

The INKEY List C-50 Serum

Active ingredients

Salicylic Acid 2%

Purpose

Acne Treatment

Uses

• for the treatment of acne.

Warnings

For external use only.

When using this product

• skin irritation and dryness is more likely to occur if you use another topical acne medication at the same time • if irritation occurs, only use one topical acne medication at a time.

Keep out of reach of children.

If swallowed, get medical help or contact a Poison Control Center right away.

If contact occurs, flush thoroughly with water. Avoid contact with eyes.

Directions

• clean the skin thoroughly before applying this product. • cover the entire affected area with a thin layer one to three times daily. • because excessive drying of the skin may occur, startwith one application daily, then gradually increase to twoor three times daily if needed or as directed by a doctor • if bothersome dryness or peeling occurs, reduce application to once a day or every other day.

Other information

Avoid storing at extreme temperatures (below 40°F and above 100°F).

Inactive ingredients

Water, Propanediol, Sodium Ascorbyl Phosphate, Ammonium Acryloyldimethyltaurate/VP Copolymer, Phenoxyethanol, Caprylyl/Capryl Glucoside, Xanthan Gum, Glycerin, Sodium Hydroxide, Madecassoside, Ethylhexylglycerin, Hydroxyacetophenone, Sodium Gluconate, Sodium Metabisulfite, Lecithin, Ascorbyl Palmitate, Nelumbo Nucifera Flower Extract, Nymphaea Coerulea Flower Extract, Tocopherol, Helianthus Annuus (Sunflower) Seed Oil.

Questions or Comments?

Call toll free (833) 981-2335